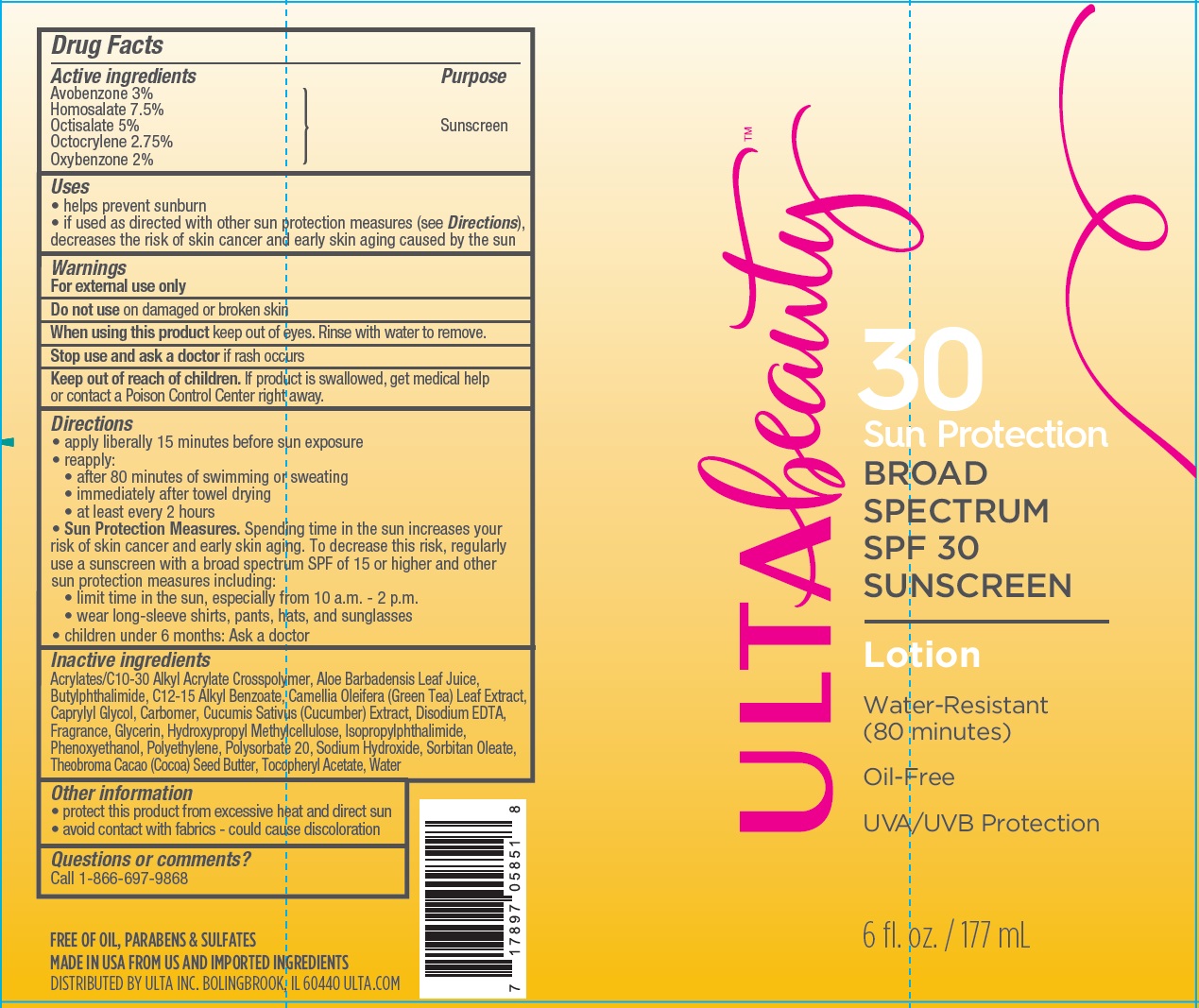 DRUG LABEL: Ulta Beauty
NDC: 58443-0244 | Form: LOTION
Manufacturer: Prime Enterprises Inc.
Category: otc | Type: HUMAN OTC DRUG LABEL
Date: 20200117

ACTIVE INGREDIENTS: OCTISALATE 50.5 mg/1 mL; OXYBENZONE 20.2 mg/1 mL; OCTOCRYLENE 27.78 mg/1 mL; AVOBENZONE 30.3 mg/1 mL; HOMOSALATE 75.75 mg/1 mL
INACTIVE INGREDIENTS: ALOE VERA LEAF; CARBOMER COPOLYMER TYPE B (ALLYL PENTAERYTHRITOL CROSSLINKED); PHENOXYETHANOL; N-BUTYLPHTHALIMIDE; ISOPROPYLPHTHALIMIDE; ALKYL (C12-15) BENZOATE; CARBOXYPOLYMETHYLENE; CAPRYLYL GLYCOL; COCOA BUTTER; .ALPHA.-TOCOPHEROL ACETATE; SORBITAN MONOOLEATE; EDETATE DISODIUM; GLYCERIN; HIGH DENSITY POLYETHYLENE; CUCUMBER; GREEN TEA LEAF; HYPROMELLOSES; POLYSORBATE 20; SODIUM HYDROXIDE; WATER

Ulta Beauty SPF 30 Broad Spectrum Sunscreen

Active Ingredients

Avobenzone 3%

Homosalate 7.5%

Octisalate 5%

Octocrylene 2.75%

Oxybenzone 2%

Purpose

Sunscreen

Uses

- helps prevent sunburn
- if used as directed with other sun protection measures (see Directions), decreases the risk of skin cancer and early skin aging caused by the sun.

Warnings

For external use only.

Do not use on damaged or broken skin

When using this product keep out of eyes. Rinse with water to remove.

Stop use and ask a doctor if rash occurs

Keep out of reach of children. If product is swallowed, get medical help or contact a Poison Control Center right away.

Directions

- apply liberally 15 minutes before sun exposure
- reapply:
- after 80 minutes of swimming or sweating
- immediately after towel drying
- at least every 2 hours
- Sun Protection Measures. Spending time in the sun increases your risk of skin cancer and early skin aging. To decrease this risk, regularly use a sunscreen with broad spectrum SPF of 15 or higher and other sun protection measures including:
- limit time in the sun, especially from 10 a.m. – 2 p.m.
- wear long-sleeve shirts, pants, hats, and sunglasses
- children under 6 months: Ask a doctor

INACTIVE INGREDIENT

Acrylates/C10-30 Alkyl Acrylate Crosspolymer, Aloe Barbadensis Leaf Juice, Butylphthalimide, C12-15 Alkyl Benzoate, Camellia Oleifera (Green Tea) Leaf Extract, Caprylyl Glycol, Carbomer, Cucumis Sativus (Cucumber) Extract, Disodium EDTA, Fragrance, Glycerin, Hydroxypropyl Methylcellulose, Isopropylphthalimide, Phenoxyethanol, Polyethylene, Polysorbate 20, Sodium Hydroxide, Sorbitan Oleate, Theobroma Cacao (Cocoa) Seed Butter, Tocopheryl Acetate, Water

Other Information

- protect this product from excessive heat and direct sun
- avoid contact with fabrics - could cause discoloration

Question or comments?

Call 1-866-697-9868